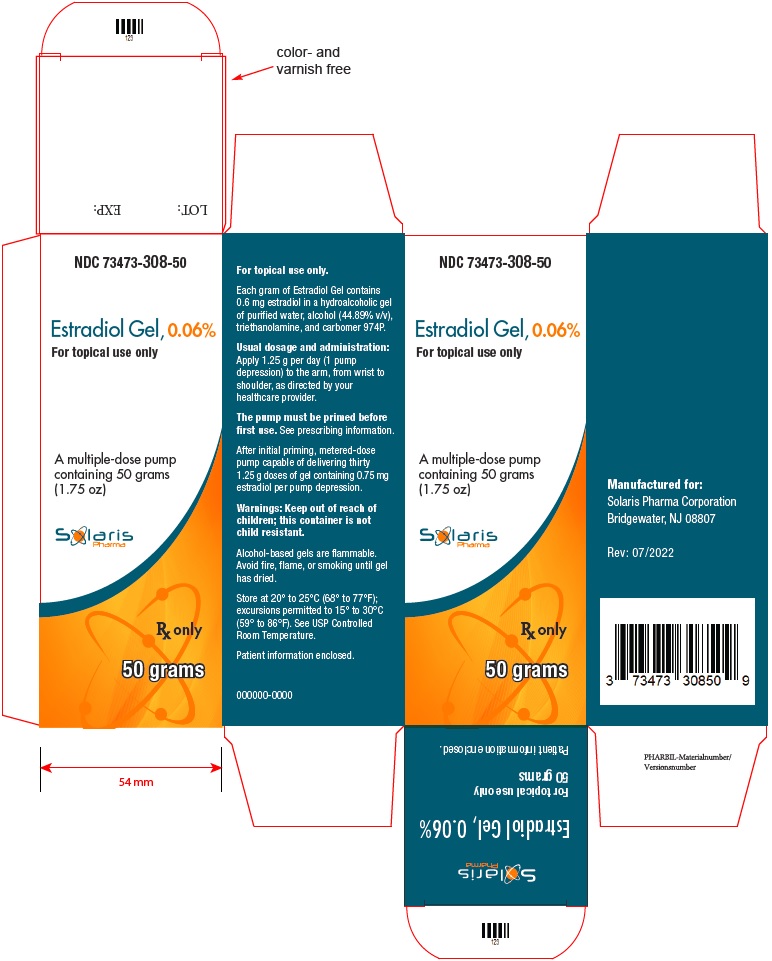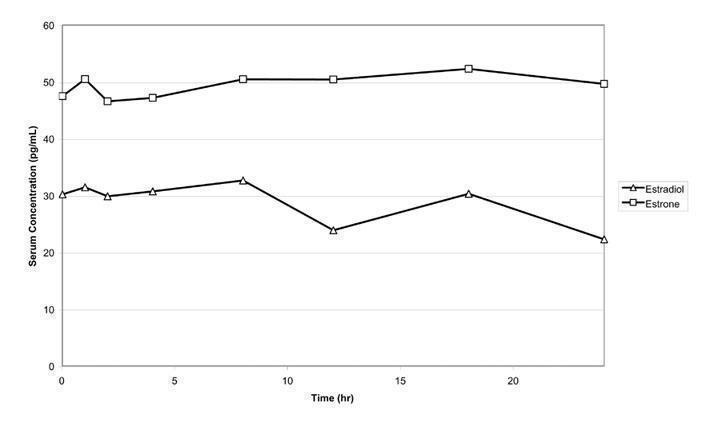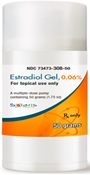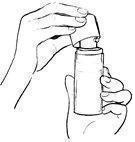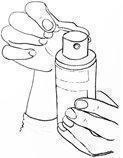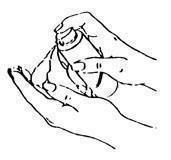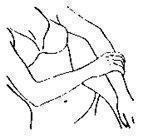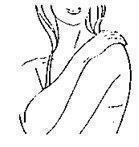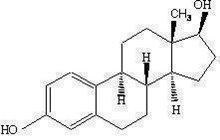 DRUG LABEL: Estradiol
NDC: 73473-308 | Form: GEL
Manufacturer: Solaris Pharma Corporation
Category: prescription | Type: Human Prescription Drug Label
Date: 20260126

ACTIVE INGREDIENTS: ESTRADIOL 0.75 mg/1.25 g

HIGHLIGHTS OF PRESCRIBING INFORMATION

These highlights do not include all the information needed to use ESTRADIOL GEL safely and effectively. See full prescribing information for ESTRADIOL GEL.
ESTRADIOL gel, for topical use
Initial U.S. Approval: 1975

RECENT MAJOR CHANGES

Warnings and Precautions, Malignant Neoplasm (5.2) 12/2023

WARNING: ENDOMETRIAL CANCER, CARDIOVASCULAR DISORDERS, PROBABLE DEMENTIA and BREAST CANCER

See full prescribing information for complete boxed warning

Estrogen-Alone Therapy

- There is an increased risk of endometrial cancer in women with a uterus who use unopposed estrogens (5.2)

- The Women’s Health Initiative (WHI) estrogen-alone substudy reported increased risks of stroke and deep vein thrombosis (DVT) (5.1)

- The WHI Memory Study (WHIMS) estrogen-alone ancillary study of WHI reported an increased risk of probable dementia in postmenopausal women 65 years of age and older (5.3)
- Do not use estrogen-alone therapy for the prevention of cardiovascular disease or dementia (5.1, 5.3)

Estrogen Plus Progestin Therapy

- The WHI estrogen plus progestin substudy reported increased risks of pulmonary embolism (PE), DVT, stroke and myocardial infarction (MI) (5.1)

- The WHI estrogen plus progestin substudy reported increased risks of invasive breast cancer (5.2)
- The WHIMS estrogen plus progestin ancillary study of WHI reported an increased risk of probable dementia in postmenopausal women 65 years of age and older (5.3)
- Do not use estrogen plus progestogen therapy for the prevention of cardiovascular disease or dementia (5.1, 5.3)

1 INDICATIONS AND USAGE

Estradiol gel, 0.06% is an estrogen indicated for:

- Treatment of moderate to severe vasomotor symptoms due to menopause (1.1)
- Treatment of moderate to severe symptoms of vulvar and vaginal atrophy due to menopause (1.2)

2 DOSAGE AND ADMINISTRATION

Metered-dose pump: Daily administration of estradiol gel, 0.06% 1.25 g per day (1 pump depression) to the arm (2.1, 2.2)

3 DOSAGE FORMS AND STRENGTHS

Gel: 1 pump depression of estradiol gel, 0.06% delivers 1.25 g of gel containing 0.75 mg estradiol

4 CONTRAINDICATIONS

- Undiagnosed abnormal genital bleeding (4, 5.2)
- Breast cancer or a history of breast cancer (4, 5.2)
- Estrogen-dependent neoplasia (4, 5.2)
- Active DVT, PE, or history of these conditions (4, 5.1)
- Active arterial thromboembolic disease (for example, stroke or MI), or a history of these conditions (4, 5.1)
- Known anaphylactic reaction, angioedema, or hypersensitivity to estradiol gel (4)
- Hepatic impairment or disease (4, 5.10)
- Protein C, protein S, or antithrombin deficiency, or other known thrombophilic disorders (4)

5 WARNINGS AND PRECAUTIONS

- Estrogens increase the risk of gallbladder disease (5.4)
- Discontinue estrogen if severe hypercalcemia, loss of vision, severe hypertriglyceridemia or cholestatic jaundice occurs (5.5, 5.6, 5.9, 5.10)
- Monitor thyroid function in women on thyroid replacement therapy (5.11, 5.20)

6 ADVERSE REACTIONS

The most common adverse reactions with estradiol gel (≥5 percent) are: headache, flatulence, and breast pain. (6.1)

To report SUSPECTED ADVERSE REACTIONS, contact Solaris Pharma Corporation at 1-833-919-0527 or FDA at 1-800-FDA-1088 or www.fda.gov/medwatch.

7 DRUG INTERACTIONS

Inducers and/or inhibitors of CYP3A4 may affect estrogen drug metabolism and decrease or increase the estrogen plasma concentration.

FULL PRESCRIBING INFORMATION

WARNING: ENDOMETRIAL CANCER, CARDIOVASCULAR DISORDERS, PROBABLE DEMENTIA and BREAST CANCER

Estrogen-Alone Therapy

Endometrial Cancer

There is an increased risk of endometrial cancer in a woman with a uterus who uses unopposed estrogens . Adding a progestogen to estrogen therapy has been shown to reduce the risk of endometrial hyperplasia, which may be a precursor to endometrial cancer. Perform adequate diagnostic measures, including directed or random endometrial sampling when indicated, to rule out malignancy in postmenopausal women with undiagnosed, persistent, or recurring abnormal genital bleeding [see Warnings and Precautions (5.2)].

Cardiovascular Disorders and Probable Dementia

The Women's Health Initiative (WHI) estrogen-alone substudy reported increased risks of stroke and deep vein thrombosis (DVT) in postmenopausal women (50 to 79 years of age) during 7.1 years of treatment with daily oral conjugated estrogens (CE) [0.625 mg]-alone, relative to placebo [see Warnings and Precautions (5.1), and Clinical Studies (14.3)].

The WHI Memory Study (WHIMS) estrogen-alone ancillary study of WHI reported an increased risk of developing probable dementia in postmenopausal women 65 years of age or older during 5.2 years of treatment with daily CE (0.625 mg)-alone, relative to placebo. It is unknown whether this finding applies to younger postmenopausal women [see Warnings and Precautions (5.3), Use in Specific Populations (8.5), and Clinical Studies (14.4)].

Do not use estrogen-alone therapy for the prevention of cardiovascular disease or dementia [see Warnings and Precautions (5.1, 5.3), and Clinical Studies (14.3, 14.4)].

Only daily oral 0.625 mg CE was studied in the estrogen-alone substudy of the WHI. Therefore, the relevance of the WHI findings regarding adverse cardiovascular events and dementia to lower CE doses, other routes of administration, or other estrogen-alone products is not known. Without such data, it is not possible to definitively exclude these risks or determine the extent of these risks for other products. Discuss with your patient the benefits and risks of estrogen-alone therapy, taking into account her individual risk profile.

Prescribe estrogens with or without progestogens at the lowest effective doses and for the shortest duration consistent with treatment goals and risks for the individual woman.

Estrogen Plus Progestin Therapy

Cardiovascular Disorders and Probable Dementia

The WHI estrogen plus progestin substudy reported increased risks of pulmonary embolism (PE), DVT, stroke and myocardial infarction (MI) in postmenopausal women (50 to 79 years of age) during 5.6 years of treatment with daily oral CE (0.625 mg) combined with medroxyprogesterone acetate (MPA) [2.5 mg], relative to placebo [see Warnings and Precautions (5.1), and Clinical Studies (14.3)].

The WHIMS estrogen plus progestin ancillary study of WHI reported an increased risk of developing probable dementia in postmenopausal women 65 years of age or older during 4 years of treatment with daily CE (0.625 mg) combined with MPA (2.5 mg), relative to placebo. It is unknown whether this finding applies to younger postmenopausal women [see Warnings and Precautions (5.3), Use in Specific Populations (8.5), and Clinical Studies (14.4)].

Do not use estrogen plus progestogen therapy for the prevention of cardiovascular disease or dementia [see Warnings and Precautions (5.1, 5.3), and Clinical Studies (14.3, 14.4)].

Breast Cancer

The WHI estrogen plus progestin substudy also demonstrated an increased risk of invasive breast cancer [see Warnings and Precautions (5.2), and Clinical Studies (14.4)].

Only daily oral 0.625 mg CE and 2.5 mg MPA were studied in the estrogen plus progestin substudy of the WHI. Therefore, the relevance of the WHI findings regarding adverse cardiovascular events, dementia and breast cancer to lower CE plus other MPA doses, other routes of administration, or other estrogen plus progestogen products is not known. Without such data, it is not possible to definitively exclude these risks or determine the extent of these risks for other products. Discuss with your patient the benefits and risks of estrogen plus progestogen therapy, taking into account her individual risk profile.

Prescribe estrogens with or without progestogens at the lowest effective doses and for the shortest duration consistent with treatment goals and risks for the individual woman.

1 INDICATIONS AND USAGE

1.1 Treatment of Moderate to Severe Vasomotor Symptoms due to Menopause

.

1.2 Treatment of Moderate to Severe Symptoms of Vulvar and Vaginal Atrophy due to Menopause

Limitation of Use

When prescribing solely for the treatment of moderate to severe symptoms of vulvar and vaginal atrophy due to menopause, first consider the use of topical vaginal products.

2 DOSAGE AND ADMINISTRATION

Generally, when estrogen is prescribed for a postmenopausal woman with a uterus, consider addition of a progestogen to reduce the risk of endometrial cancer. Generally, a woman without a uterus does not need to use a progestogen in addition to her estrogen therapy. In some cases, however, hysterectomized women with a history of endometriosis may need a progestogen [see Warnings and Precautions (5.2, 5.14)].

Use estrogen-alone, or in combination with a progestogen at the lowest effective dose and for the shortest duration consistent with treatment goals and risks for the individual woman. Reevaluate postmenopausal women periodically as clinically appropriate to determine if treatment is still necessary.

2.1 Treatment of Moderate to Severe Vasomotor Symptoms due to Menopause

Estradiol gel, 0.06% 1.25 g per day is the single approved dose for the treatment of moderate to severe vasomotor symptoms due to menopause. The lowest effective dose of estradiol gel, 0.06% for this indication has not been determined.

Before using the canister for the first time, it must be primed. Remove the large canister cover, and fully depress the pump 5 times. Discard the unused gel by thoroughly rinsing down the sink or placing it in the household trash. After priming, the pump is ready to use.

The recommended area of application is the arm. Apply a thin layer over the entire arm on the inside and outside from wrist to shoulder.

2.2 Treatment of Moderate to Severe Symptoms of Vulvar and Vaginal Atrophy due to Menopause

Estradiol gel, 0.06% 1.25 g per day is the single approved dose for the treatment of moderate to severe symptoms of vulvar and vaginal atrophy due to menopause. The lowest effective dose of estradiol gel, 0.06% for this indication has not been determined. When prescribing solely for the treatment of moderate to severe symptoms of vulvar and vaginal atrophy, first consider the use of topical vaginal products.

Before using the canister for the first time, it must be primed. Remove the large canister cover, and fully depress the pump 5 times. Discard the unused gel by thoroughly rinsing down the sink or placing it in the household trash. After priming, the pump is ready to use.

The recommended area of application is the arm. Apply a thin layer over the entire arm on the inside and outside from wrist to shoulder.

3 DOSAGE FORMS AND STRENGTHS

Estradiol gel, 0.06% is an estradiol transdermal gel. One pump depression delivers 1.25 g of gel that contains 0.75 mg estradiol.

4 CONTRAINDICATIONS

Estradiol gel is contraindicated in women with any of the following conditions:

• Undiagnosed abnormal genital bleeding [see Warnings and Precautions (5.2)]
• Breast cancer or a history of breast cancer [see Warnings and Precautions (5.2)]
• Estrogen-dependent neoplasia [see Warnings and Precautions (5.2)]
• Active DVT, PE, or history of these conditions [see Warnings and Precautions (5.1)]
• Active arterial thromboembolic disease (for example, stroke or MI), or a history of these conditions [see Warnings and Precautions (5.1)]
• Known anaphylactic reaction, angioedema, or hypersensitivity to estradiol gel
• Hepatic impairment or disease
• Protein C, protein S, or antithrombin deficiency, or other known thrombophilic disorders

5 WARNINGS AND PRECAUTIONS

5.1 Cardiovascular Disorders

Increased risks of stroke and DVT are reported with estrogen-alone therapy. Increased risks of PE, DVT, stroke and MI are reported with estrogen plus progestin therapy. Immediately discontinue estrogen with or without progestogen if any of these occur or are suspected.

Manage appropriately any risk factors for arterial vascular disease (for example, hypertension, diabetes mellitus, tobacco use, hypercholesterolemia, and obesity) and/or venous thromboembolism (VTE) (for example, personal history or family history of VTE, obesity, and systemic lupus erythematosus).

Stroke

The WHI estrogen-alone substudy reported a statistically significant increased risk of stroke in women 50 to 79 years of age receiving daily CE (0.625 mg)-alone compared to women in the same age group receiving placebo (45 versus 33 per 10,000 women-years, respectively). The increase in risk was demonstrated in year 1 and persisted [see Clinical Studies (14.3)]. Immediately discontinue estrogen-alone therapy if a stroke occurs or is suspected.

Subgroup analysis of women 50 to 59 years of age suggest no increased risk of stroke for those women receiving CE (0.625 mg)-alone versus those receiving placebo (18 versus 21 per 10,000 women-years).^1

The WHI estrogen plus progestin substudy reported a statistically significant increased risk of stroke in women 50 to 79 years of age receiving daily CE (0.625 mg) plus MPA (2.5 mg) compared to women in the same age group receiving placebo (33 versus 25 per 10,000 women-years) [see Clinical Studies (14.3)].The increase in risk was demonstrated after the first year and persisted.^1 Immediately discontinue estrogen with or without progestogen therapy if a stroke occurs or is suspected.

Coronary Heart Disease

The WHI estrogen-alone substudy reported no overall effect on coronary heart disease (CHD) events (defined as nonfatal MI, silent MI, or CHD death) in women receiving estrogen-alone compared to placebo^2 [see Clinical Studies (14.3)].

Subgroup analyses of women 50 to 59 years of age, who were less than 10 years since menopause, suggest a reduction (not statistically significant) of CHD events in those women receiving CE (0.625 mg)-alone compared to placebo) (8 versus 16 per 10,000 women-years).^1

The WHI estrogen plus progestin substudy reported an increased risk (not statistically significant) of CHD events in those women receiving daily CE (0.625 mg) plus MPA (2.5 mg) compared to women receiving placebo (41 versus 34 per 10,000 women-years).^1 An increase in relative risk was demonstrated in year 1, and a trend toward decreasing relative risk was reported in years 2 through 5 [see Clinical Studies (14.3)].

In postmenopausal women with documented heart disease (n = 2,763, average 66.7 years of age), in a controlled clinical trial of secondary prevention of cardiovascular disease (Heart and Estrogen/Progestin Replacement Study; HERS), treatment with daily CE (0.625 mg) plus MPA (2.5 mg) demonstrated no cardiovascular benefit. During an average follow-up of 4.1 years, treatment with CE plus MPA did not reduce the overall rate of CHD events in postmenopausal women with established CHD. There were more CHD events in the CE plus MPA-treated group than in the placebo group in year 1, but not during the subsequent years. Two thousand, three hundred twenty-one (2,321) women from the original HERS trial agreed to participate in an open-label extension of the original HERS, HERS II. Average follow-up in HERS II was an additional 2.7 years, for a total of 6.8 years overall. Rates of CHD events were comparable among women in the CE plus MPA group and the placebo group in HERS, HERS II, and overall.

Venous Thromboembolism

In the WHI estrogen-alone substudy, the risk of VTE (DVT and PE) was increased for women receiving daily CE (0.625 mg)-alone compared to placebo (30 versus 22 per 10,000 women-years), although only the increased risk of DVT reached statistical significance (23 versus 15 per 10,000 women-years). The increase in VTE risk was demonstrated during the first 2 years^3 [see Clinical Studies (14.3)]. Immediately discontinue estrogen-alone therapy if a VTE occurs or is suspected.

The WHI estrogen plus progestin substudy reported a statistically significant 2-fold greater rate of VTE in women receiving daily CE (0.625 mg) plus MPA (2.5 mg) compared to women receiving placebo (35 versus 17 per 10,000 women-years). Statistically significant increases in risk for both DVT (26 versus 13 per 10,000 women-years) and PE (18 versus 8 per 10,000 women-years) were also demonstrated. The increase in VTE risk was demonstrated during the first year and persisted^4 [see Clinical Studies (14.3)]. Immediately discontinue estrogen plus progestogen therapy if a VTE occurs or is suspected.

If feasible, discontinue estrogens at least 4 to 6 weeks before any surgery of the type associated with an increased risk of thromboembolism, or during periods of prolonged immobilization.

5.2 Malignant Neoplasms

Endometrial Cancer

An increased risk of endometrial cancer has been reported with the use of unopposed estrogen therapy in women with a uterus. The reported endometrial cancer risk among unopposed estrogen users is about 2- to 12-fold greater than in nonusers, and appears dependent on duration of treatment and on estrogen dose. Most studies show no significant increased risk associated with use of estrogens for less than 1 year. The greatest risk appears to be associated with prolonged use, with increased risks of 15- to 24-fold for 5 to 10 years or more, and this risk has been shown to persist for at least 8 to 15 years after estrogen therapy is discontinued.

Clinical surveillance of all women using estrogen-alone or estrogen plus progestogen therapy is important. Perform adequate diagnostic measures, including directed or random endometrial sampling when indicated, to rule out malignancy in postmenopausal women with undiagnosed persistent or recurring abnormal genital bleeding with unknown etiology.

There is no evidence that the use of natural estrogens results in a different endometrial risk profile than synthetic estrogens of equivalent estrogen dose. Adding a progestogen to estrogen therapy in postmenopausal women has been shown to reduce the risk of endometrial hyperplasia, which may be a precursor to endometrial cancer.

Breast Cancer

The WHI substudy of daily CE (0.625 mg)-alone provided information about breast cancer in estrogen-alone users. In the WHI estrogen-alone substudy, after an average follow-up of 7.1 years, daily CE(0.625 mg)-alone was not associated with an increased risk of invasive breast cancer [relative risk (RR) 0.8])^5 compared to placebo [see Clinical Studies (14.3)].

After a mean follow-up of 5.6 years, the WHI substudy of daily CE (0.625 mg) plus MPA (2.5 mg) reported an increased risk of invasive breast cancer in women who took daily CE plus MPA compared to placebo.

In this substudy, prior use of estrogen-alone or estrogen plus progestin therapy was reported by 26 percent of the women. The relative risk of invasive breast cancer was 1.24, and the absolute risk was 41 versus 33 cases per 10,000 women-years, for CE plus MPA compared with placebo [see Clinical Studies (14.3)]. Among women who reported prior use of hormone therapy, the relative risk of invasive breast cancer was 1.86, and the absolute risk was 46 versus 25 cases per 10,000 women-years, for CE plus MPA compared with placebo. Among women who reported no prior use of hormone therapy, the relative risk of invasive breast cancer was 1.09, and the absolute risk was 40 versus 36 cases per 10,000 women-years for CE plus MPA compared with placebo. In the same substudy, invasive breast cancers were larger, were more likely to be node positive, and were diagnosed at a more advanced stage in the CE (0.625 mg) plus MPA (2.5 mg) group compared with the placebo group. Metastatic disease was rare, with no apparent difference between the two groups. Other prognostic factors, such as histologic subtype, grade and hormone receptor status did not differ between the groups^6 [see Clinical Studies (14.3)].

Consistent with the WHI clinical trials, observational studies have also reported an increased risk of breast cancer with estrogen plus progestin therapy, and a smaller increased risk for estrogen-alone therapy, after several years of use. One large meta-analysis of prospective cohort studies reported increased risks that were dependent upon duration of use and could last up to >10 years after discontinuation of estrogen plus progestin therapy and estrogen-alone therapy. Extension of the WHI trials also demonstrated increased breast cancer risk associated with estrogen plus progestin therapy. Observational studies also suggest that the risk of breast cancer was greater, and became apparent earlier, with estrogen plus progestin therapy as compared to estrogen-alone therapy. However, these studies have not generally found significant variation in the risk of breast cancer among different estrogen plus progestin combinations, doses, or routes of administration.

The use of estrogen-alone and estrogen plus progestin therapy has been reported to result in an increase in abnormal mammograms requiring further evaluation.

Have all women receive yearly breast examinations by a healthcare provider and perform monthly breast self-examinations. In addition, base the scheduling of mammography examinations on patient age, risk factors, and prior mammogram results.

Ovarian Cancer

The CE plus MPA substudy of WHI reported that estrogen plus progestin increased the risk of ovarian cancer. After an average follow-up of 5.6 years, the relative risk for CE plus MPA versus placebo was 1.58 (95 percent CI, 0.77-3.24), but it was not statistically significant. The absolute risk for CE plus MPA versus placebo was 4 versus 3 cases per 10,000 women-years.^7

A meta-analysis of 17 prospective and 35 retrospective epidemiology studies found that women who used hormonal therapy for menopausal symptoms had an increased risk for ovarian cancer. The primary analysis, using case-control comparisons, included 12,110 cancer cases from the 17 prospective studies. The relative risks associated with current use of hormonal therapy was 1.41 (95% confidence interval [CI] 1.32 to 1.50); there was no difference in the risk estimates by duration of the exposure (less than 5 years [median of 3 years] vs. greater than 5 years [median 10 years] of use before the cancer diagnosis). The relative risk associated with combined current and recent use (discontinued use within 5 years before cancer diagnosis) was 1.37 (95% CI 1.27 – 1.48), and the elevated risk was significant for both estrogen-alone and estrogen plus progestin products. The exact duration of hormone therapy use associated with an increased risk of ovarian cancer, however, is unknown.

5.3 Probable Dementia

In the WHI Memory Study (WHIMS) estrogen-alone ancillary study, a population of 2,947 hysterectomized women 65 to 79 years of age was randomized to daily CE (0.625 mg)-alone or placebo.

After an average follow-up of 5.2 years, 28 women in the estrogen-alone group and 19 women in the placebo group were diagnosed with probable dementia. The relative risk of probable dementia for CE-alone versus placebo was 1.49 (95 percent CI, 0.83-2.66). The absolute risk of probable dementia for CE-alone versus placebo was 37 versus 25 cases per 10,000 women-years^8 [see Use in Specific Populations (8.5), and Clinical Studies (14.4)].

In the WHIMS estrogen plus progestin ancillary study, a population of 4,532 postmenopausal women 65 to 79 years of age was randomized to daily CE (0.625 mg) plus MPA (2.5 mg) or placebo. After an average follow-up of 4 years, 40 women in the CE plus MPA group and 21 women in the placebo group were diagnosed with probable dementia. The relative risk of probable dementia for CE plus MPA versus placebo was 2.05 (95 percent CI, 1.21-3.48). The absolute risk of probable dementia for CE plus MPA versus placebo was 45 versus 22 cases per 10,000 women-years^8 [see Use in Specific Populations (8.5), and Clinical Studies (14.4)].

When data from the two populations in the WHIMS estrogen-alone and estrogen plus progestin ancillary studies were pooled as planned in the WHIMS protocol, the reported overall relative risk for probable dementia was 1.76 (95 percent CI, 1.19-2.60). Since both ancillary studies were conducted in women 65 to 79 years of age, it is unknown whether these findings apply to younger postmenopausal women [see Use in Specific Populations (8.5), and Clinical Studies (14.4)].

5.4 Gallbladder Disease

A 2- to 4-fold increase in the risk of gallbladder disease requiring surgery in postmenopausal women receiving estrogens has been reported.

5.5 Hypercalcemia

Estrogen administration may lead to severe hypercalcemia in women with breast cancer and bone metastases. Discontinue estrogens, including estradiol gel if hypercalcemia occurs, and take appropriate measures to reduce the serum calcium level.

5.6 Visual Abnormalities

Retinal vascular thrombosis has been reported in women receiving estrogens. Discontinue estradiol gel pending examination if there is sudden partial or complete loss of vision or a sudden onset of proptosis, diplopia, or migraine. Permanently discontinue estrogens, including estradiol gel if examination reveals papilledema or retinal vascular lesions.

5.7 Addition of a Progestogen When a Woman Has Not Had a Hysterectomy

Studies of the addition of a progestogen for 10 or more days of a cycle of estrogen administration, or daily with estrogen in a continuous regimen, have reported a lowered incidence of endometrial hyperplasia than would be induced by estrogen treatment alone. Endometrial hyperplasia may be a precursor to endometrial cancer.

There are, however, possible risks that may be associated with the use of progestogens with estrogens compared to estrogen-alone regimens. These include an increased risk of breast cancer.

5.8 Elevated Blood Pressure

In a small number of case reports, substantial increases in blood pressure have been attributed to idiosyncratic reactions to estrogens. In a large, randomized, placebo-controlled clinical trial, a generalized effect of estrogens on blood pressure was not seen.

5.9 Exacerbation of Hypertriglyceridemia

In women with pre-existing hypertriglyceridemia, estrogen therapy may be associated with elevations of plasma triglycerides leading to pancreatitis. Discontinue estradiol gel if pancreatitis occurs.

5.10 Hepatic Impairment and/or Past History of Cholestatic Jaundice

Estrogens may be poorly metabolized in women with hepatic impairment. Exercise caution in any woman with a history of cholestatic jaundice associated with past estrogen use or with pregnancy. In the case of recurrence of cholestatic jaundice, discontinue estradiol gel.

5.11 Exacerbation of Hypothyroidism

Estrogen administration leads to increased thyroid-binding globulin (TBG) levels. Women with normal thyroid function can compensate for the increased TBG by making more thyroid hormone, thus maintaining free T4 and T3 serum concentrations in the normal range. Women dependent on thyroid hormone replacement therapy who are also receiving estrogens may require increased doses of their thyroid replacement therapy. Monitor thyroid function in these women during treatment with estradiol gel to maintain their free thyroid hormone levels in an acceptable range.

5.12 Fluid Retention

Estrogens may cause some degree of fluid retention. Monitor any woman with a condition(s) that might predispose her to fluid retention, such as cardiac or renal impairment. Discontinue estrogen-alone therapy, including estradiol gel, with evidence of medically concerning fluid retention.

5.13 Hypocalcemia

Estrogen-induced hypocalcemia may occur in women with hypoparathyroidism. Consider whether the benefits of estrogen therapy, including estradiol gel, outweigh the risks in such women.

5.14 Exacerbation of Endometriosis

A few cases of malignant transformation of residual endometrial implants have been reported in women treated post-hysterectomy with estrogen-alone therapy. Consider the addition of progestogen therapy for women known to have residual endometriosis post-hysterectomy.

5.15 Hereditary Angioedema

Exogenous estrogens may exacerbate symptoms of angioedema in women with hereditary angioedema. Consider whether the benefits of estrogen therapy, including estradiol gel, outweigh the risks in such women.

5.16 Exacerbation of Other Conditions

Estrogen therapy, including estradiol gel, may cause an exacerbation of asthma, diabetes mellitus, epilepsy, migraine, porphyria, systemic lupus erythematosus, and hepatic hemangiomas. Consider whether the benefits of estrogen therapy outweigh the risks in women with such conditions.

5.17 Alcohol-based Gels Are Flammable

Avoid fire, flame, or smoking until estradiol gel has dried.

5.18 Moisturizer Lotion Application

Use of moisturizing lotion one hour after application of estradiol gel significantly increased estradiol absorption [see Clinical Pharmacology(12.3)].

5.19 Laboratory Tests

Serum follicle stimulating hormone (FSH) and estradiol levels have not been shown to be useful in the management of postmenopausal women with moderate to severe vasomotor symptoms and moderate to severe symptoms of vulvar and vaginal atrophy.

5.20 Drug-Laboratory Test Interactions

- Accelerated prothrombin time, partial thromboplastin time, and platelet aggregation time; increased platelet count; increased factors II, VII antigen, VIII antigen, VIII coagulant activity, IX, X, XII, VII-X complex, II-VII-X complex, and beta-thromboglobulin; decreased levels of anti-factor Xa and antithrombin III, decreased antithrombin III activity; increased levels of fibrinogen and fibrinogen activity; increased plasminogen antigen and activity.

- Increased thyroid-binding globulin (TBG) levels leading to increased circulating total thyroid hormone levels, as measured by protein-bound iodine (PBI), T4 levels (by column or by radioimmunoassay) or T3 levels by radioimmunoassay. T3 resin uptake is decreased, reflecting the elevated TBG. Free T4 and T3 concentrations are unaltered. Women on thyroid-replacement therapy may require higher doses of thyroid hormone.

- Other binding proteins may be elevated in serum (for example, corticosteroid-binding globulin [CBG], sex hormone-binding globulin [SHBG]), leading to increased total circulating corticosteroids and sex steroids, respectively. Free hormone concentrations, such as testosterone and estradiol, may be decreased. Other plasma proteins may be increased (angiotensinogen/renin substrate, alpha-1-antitrypsin, ceruloplasmin).

- Increased plasma high-density lipoprotein (HDL) and HDL2 cholesterol subfraction concentrations, reduced low-density lipoprotein (LDL) cholesterol concentration, increased triglyceride levels.

- Impaired glucose tolerance.

6 ADVERSE REACTIONS

The following serious adverse reactions are discussed elsewhere in the labeling:

- Cardiovascular Disorders [see Boxed Warning, and Warnings and Precautions (5.1)]
- Malignant Neoplasms [see Boxed Warning, and Warnings and Precautions (5.2)]

6.1 Clinical Trials Experience

Because clinical trials are conducted under widely varying conditions, adverse reaction rates observed in the clinical trials of a drug cannot be directly compared to rates in the clinical trials of another drug and may not reflect the rates observed in clinical practice.

Estradiol gel was studied in 2 well-controlled, 12-week clinical trials. Incidence of adverse drug reactions ≥5 percent for 1.25 g estradiol gel, 0.06% and placebo is given in Table 1.

Table 1: Incidence of Adverse Drug Reactions ≥5 Percent Occurrence in the Estradiol Gel Treatment Group for the Intent-to-Treat Safety Population in 2 Well-controlled Clinical Studies (Expressed as Percent of Treatment Group)
Body System/ Adverse Drug Reactions | Estradiol Gel, 0.06% 1.25 g /day (n=168) | Placebo (n=73)
BODY AS A WHOLE
Headache | 9.5 | 2.7
DIGESTIVE SYSTEM
Flatulence | 5.4 | 4.1
UROGENITAL SYSTEM
Breast pain | 10.7 | 8.2

In 2 controlled clinical trials, application site reactions were reported by 0.6 percent of patients who received 1.25 g of estradiol gel. Other skin reactions, such as pruritus and rash, were also noted.

6.2 Postmarketing Experience

The following adverse reactions have been identified during post-approval use of estradiol gel. Because these reactions are reported voluntarily from a population of uncertain size, it is not always possible to reliably estimate their frequency or establish a causal relationship to drug exposure.

Genitourinary system

Endometrial cancer

Breast

Pain; tenderness; breast cancer

Cardiovascular

Deep vein thrombosis; myocardial ischemia; phlebitis

Gastrointestinal

Nausea; abdominal distension; diarrhea; stomach discomfort

Skin

Alopecia; rash; pruritus; application site: dryness, pain, discoloration, reaction, rash

Eyes

Retinal vein occlusion

Central nervous system

Headache; dizziness; insomnia; hypoesthesia; meningioma; aphasia; bradyphrenia; paresthesia

Miscellaneous

Drug ineffective; hot flush; arthralgia; night sweats; drug effect decreased; pain in extremity; fatigue; weight increased; pain; hypersensitivity; dyspnea; malignant mesenchymoma; angioedema; hepatitis acute; face edema; accidental exposure; myoclonus; gait disturbance; flushing

7 DRUG INTERACTIONS

In vitro and in vivo studies have shown that estrogens are metabolized partially by cytochrome P450 3A4 (CYP3A4). Therefore, inducers or inhibitors of CYP3A4 may affect estrogen drug metabolism. Inducers of CYP3A4, such as St. John’s wort (Hypericum perforatum) preparations, phenobarbital, carbamazepine, and rifampin, may reduce plasma concentrations of estrogens, possibly resulting in a decrease in therapeutic effects and/or changes in the uterine bleeding profile. Inhibitors of CYP3A4 such as erythromycin, clarithromycin, ketoconazole, itraconazole, ritonavir, and grapefruit juice may increase plasma concentrations of estrogen and may result in adverse reactions.

8 USE IN SPECIFIC POPULATIONS

8.1 Pregnancy

Risk Summary
Estradiol gel is not indicated for use in pregnancy. There are no data with the use of estradiol gel in pregnant women, however, epidemiologic studies and meta-analysis have not found an increased risk of genital or non-genital birth defects (including cardiac anomalities and limb-reduction defects) following exposure to combined hormonal contraceptives (estrogens and progestins) before conception or during early pregnancy.

In the U.S. general population, the estimated background rate of major birth defects and miscarriage in clinically recognized pregnancies is 2% to 4% and 15% to 20%, respectively.

8.3 Lactation

Estrogens are present in human milk and can reduce milk production in breast-feeding women. This reduction can occur at any time but is less likely to occur once breast-feeding is well established. The development and health benefits of breastfeeding should be considered along with the mother’s clinical need for estradiol gel and any potential adverse effects on the breastfed child from estradiol gel or from the underlying maternal condition.

8.4 Pediatric Use

Estradiol gel is not indicated for use in pediatric patients. Clinical studies have not been conducted in the pediatric population.

8.5 Geriatric Use

There have not been sufficient numbers of geriatric women involved in clinical studies utilizing estradiol gel to determine whether those over 65 years of age differ from younger subjects in their response to estradiol gel.

The Women’s Health Initiative Studies

In the WHI estrogen-alone substudy (daily CE [0.625 mg]-alone versus placebo), there was a higher relative risk of stroke in women greater than 65 years of age [see Warnings and Precautions (5.1) and Clinical Studies (14.3)].

In the WHI estrogen plus progestin substudy (daily CE [0.625 mg] plus MPA [2.5 mg] versus placebo), there was a higher relative risk of nonfatal stroke and invasive breast cancer in women greater than 65 years of age [see Warnings and Precautions (5.1) and Clinical Studies (14.3)].

The Women’s Health Initiative Memory Study

In the WHIMS ancillary studies of postmenopausal women 65 to 79 years of age, there was an increased risk of developing probable dementia in women receiving estrogen-alone or estrogen plus progestin when compared to placebo [see Warnings and Precautions (5.3), and Clinical Studies (14.4)].

Since both ancillary studies were conducted in women 65 to 79 years of age, it is unknown whether these findings apply to younger postmenopausal women^8 [see Warnings and Precautions (5.3), and Clinical Studies (14.4)].

10 OVERDOSAGE

Overdosage of estrogen may cause nausea, vomiting, breast tenderness, abdominal pain, drowsiness and fatigue, and withdrawal bleeding may occur in women. Treatment of overdose consists of discontinuation of estradiol gel therapy with institution of appropriate symptomatic care.

11 DESCRIPTION

Estradiol gel contains 0.06 percent estradiol in an absorptive hydroalcoholic gel base for topical application. It is a clear, colorless gel, which is odorless when dry. One pump depression of estradiol gel, 0.06% delivers 1.25 g of gel containing 0.75 mg estradiol.

Estradiol is a white crystalline powder, chemically described as estra-1,3,5(10)-triene-3,17β-diol. It has an empirical formula of C18H24O2 and molecular weight of 272.39. The structural formula is:

The active component of the gel is estradiol. The remaining components of the gel (purified water, alcohol (44.89% v/v), triethanolamine and carbomer 974P) are pharmacologically inactive.

12 CLINICAL PHARMACOLOGY

12.1 Mechanism of Action

Endogenous estrogens are largely responsible for the development and maintenance of the female reproductive system and secondary sexual characteristics. Although circulating estrogens exist in a dynamic equilibrium of metabolic interconversions, estradiol is the principal intracellular human estrogen and is substantially more potent than its metabolites, estrone and estriol, at the receptor level.

The primary source of estrogen in normally cycling adult women is the ovarian follicle, which secretes 70 to 500 mcg of estradiol daily, depending on the phase of the menstrual cycle. After menopause, most endogenous estrogen is produced by conversion of androstenedione, secreted by the adrenal cortex, to estrone in the peripheral tissues. Thus, estrone and the sulfate-conjugated form, estrone sulfate, are the most abundant circulating estrogens in postmenopausal women.

Estrogens act through binding to nuclear receptors in estrogen-responsive tissues. To date, 2 estrogen receptors have been identified. These vary in proportion from tissue to tissue.

Circulating estrogens modulate the pituitary secretion of the gonadotropins, luteinizing hormone (LH) and FSH through a negative feedback mechanism. Estrogens act to reduce the elevated levels of these hormones seen in postmenopausal women.

12.2 Pharmacodynamics

Generally, a serum estrogen concentration does not predict an individual woman’s therapeutic response to estradiol gel nor her risk for adverse outcomes. Likewise, exposure comparisons across different estrogen products to infer efficacy or safety for the individual woman may not be valid.

12.3 Pharmacokinetics

Absorption

Estradiol is transported across intact skin and into the systemic circulation by a passive diffusion process. The rate of diffusion across the stratum corneum is the rate-limiting factor. When estradiol gel is applied to the skin, it dries in 2 to 5 minutes.

Estradiol gel 1.25 g (containing 0.75 mg of estradiol) was administered to 24 postmenopausal women once daily on the posterior surface of 1 arm from wrist to shoulder for 14 consecutive days. Mean maximal serum concentrations of estradiol and estrone on Day 14 were 46.4 pg/mL and 64.2 pg/mL, respectively. The time-averaged serum estradiol and estrone concentrations over the 24-hour dose interval after administration of 1.25 g estradiol gel on Day 14 are 28.3 pg/mL and 48.6 pg/mL, respectively. Mean concentration-time profiles for unadjusted estradiol and estrone on Day 14 are shown in Figure 1.

Figure 1: Mean Serum Concentration-time Profiles for Unadjusted Estradiol and Estrone After Multiple-dose Applications of 1.25 g Estradiol Gel, 0.06% for 14 Days

The serum concentrations of estradiol following 2.5 g estradiol gel applications (1.25 g on each arm from wrist to shoulder) appeared to reach steady state after the third daily application.

Distribution

The distribution of exogenous estrogens is similar to that of endogenous estrogens. Estrogens are widely distributed in the body and are generally found in higher concentrations in the sex hormone target organs. Estrogens circulate in blood largely bound to SHBG and albumin.

Metabolism

Exogenous estrogens are metabolized in the same manner as endogenous estrogens. Circulating estrogens exist in a dynamic equilibrium of metabolic interconversions. These transformations take place mainly in the liver. Estradiol is converted reversibly to estrone, and both can be converted to estriol, which is a major urinary metabolite. Estrogens also undergo enterohepatic recirculation via sulfate and glucuronide conjugation in the liver, biliary secretion of conjugates into the intestine, and hydrolysis in the intestine followed by reabsorption. In postmenopausal women, a significant proportion of the circulating estrogens exist as sulfate conjugates, especially estrone sulfate, which serves as a circulating reservoir for the formation of more active estrogens. Although the clinical significance has not been determined, estradiol from estradiol gel does not go through first-pass liver metabolism.

Excretion

Estradiol, estrone, and estriol are excreted in the urine along with glucuronide and sulfate conjugates.

The apparent terminal exponential half-life for estradiol was about 36 hours following administration of 1.25 g estradiol gel.

Effect of Application Site Washing

The effect of application site washing on the serum concentrations of estradiol was determined in 24 healthy postmenopausal women who applied 1.25 g of estradiol gel once daily for 14 consecutive days. Site washing 1 hour after the application resulted in a 22 percent mean decrease in average 24-hour serum concentrations of estradiol.

Potential for Estradiol Transfer

The effect of estradiol transfer was evaluated in 24 healthy postmenopausal women who topically applied 1.25 g of estradiol gel once daily on the posterior surface of 1 arm from wrist to shoulder for a period of 14 consecutive days. On each day, 1 hour after gel application, a cohort of 24 non-dosed healthy postmenopausal females directly contacted the dosed cohort at the site of gel application for 15 minutes. No change in endogenous mean serum concentrations of estradiol was observed in the non-dosed cohort after direct skin-to-skin contact with subjects administered estradiol gel.

Effect of Moisturizer Lotion/Sunscreen on Estradiol Absorption

The effect of sunscreen and moisturizer lotion on estradiol absorption from 0.06% estradiol topical gel was evaluated in a randomized, open-label, three-period crossover study in 42 healthy postmenopausal women. The study results showed that repeated daily application of sunscreen for 7 days at 1 hour after the administration of 0.06% estradiol topical gel decreased the mean AUC0-24h and Cmax of estradiol by 16%. Repeated daily application of moisturizer lotion for 7 days at 1 hour after the administration of 0.06% estradiol topical gel increased the mean AUC0-24h and Cmax of estradiol by 38% and 73%, respectively.

The effect of daily application of sunscreen/moisturizer lotion on estradiol absorption, when sunscreen/moisturizer lotion is applied before administration of 0.06% estradiol topical gel, was not studied.

13 NONCLINICAL TOXICOLOGY

13.1 Carcinogenesis, Mutagenesis, Impairment of Fertility

Long-term, continuous administration of natural and synthetic estrogens in certain animal species increases the frequency of carcinomas of the breast, uterus, cervix, vagina, testis, and liver.

14 CLINICAL STUDIES

14.1 Effects on Vasomotor Symptoms in Postmenopausal Women

In a placebo-controlled study, 145 postmenopausal women between 29 and 67 years of age (81.4 percent were White) were randomly assigned to receive 1.25 g of estradiol gel (containing 0.75 mg of estradiol) or placebo gel for 12 weeks. Efficacy was assessed at 4 and 12 weeks of treatment. A statistically significant reduction in the frequency and severity of moderate to severe hot flushes was shown at Weeks 4 and 12. (See Table 2)

Table 2: Mean Change from Baseline in the Number and Severity of Hot Flushes per Day, ITT Population, LOCF
 | Number of Hot Flushes/Day (Moderate to Severe) |  | Severity Score/Day (Mild, Moderate, Severe)
 | Placebo n=73 | Estradiol Gel, 0.06% 1.25 g n=72 | Placebo n=73 | Estradiol Gel, 0.06% 1.25 g n=72
Baseline Mean (SD) | 11.01 (5.66) | 10.33 (3.07) | 2.30 (0.24) | 2.36 (0.29)
Week 4* Mean (SD) Mean change from baseline (SD) Diff. vs placebo P value † | 5.95 (5.17) -5.06 (4.91) | 4.43 (4.13) -5.91 (3.68) 0.85 0.019 ‡ | 2.00 (0.63) -0.31 (0.62) | 1.73 (0.73) -0.63 (0.71) 0.32 0.005‡
Week 12* Mean (SD) Mean change from baseline (SD) Diff. vs placebo P value † | 5.17 (6.52) -5.84 (4.52) | 2.79 (3.70) -7.55 (3.52) 1.71 0.043 ‡ | 1.76 (0.84) -0.54 (0.84) | 1.33 (0.97) -1.03 (0.94) 0.49 <0.001‡
*Primary timepoint.
† P values from Elteren’s nonparametric test.
‡ Statistically significantly different from placebo.

14.2 Effects on Vulvar and Vaginal Atrophy in Postmenopausal Women

Results of the vaginal wall cytology showed a significant (P≤0.001) increase from baseline in the percent of superficial epithelial cells at Week 12 for 1.25 g estradiol gel. In contrast, no significant change from baseline was observed in the placebo group.

14.3 Women’s Health Initiative Studies

The WHI enrolled approximately 27,000 predominantly healthy postmenopausal women in two substudies to assess the risks and benefits of daily oral CE (0.625 mg)-alone or in combination with MPA (2.5 mg) compared to placebo in the prevention of certain chronic diseases. The primary endpoint was the incidence of CHD (defined as nonfatal MI, silent MI, and CHD death), with invasive breast cancer as the primary adverse outcome. A “global index” included the earliest occurrence of CHD, invasive breast cancer, stroke, PE, endometrial cancer (only in the CE plus MPA substudy), colorectal cancer, hip fracture, or death due to other causes. These substudies did not evaluate the effects of CE-alone or CE plus MPA on menopausal symptoms.

WHI Estrogen-Alone Substudy

The WHI estrogen-alone substudy was stopped early because an increased risk of stroke was observed, and it was deemed that no further information would be obtained regarding the risks and benefits of estrogen-alone in predetermined primary endpoints. Results of the estrogen-alone substudy, which included 10,739 women (average 63 years of age, range 50-79; 75.3 percent White, 15.1 percent Black, 6.1 percent Hispanic, 3.6 percent Other), after an average follow-up of 7.1 years are presented in Table 3.

Table 3: Relative and Absolute Risk Seen in the Estrogen-Alone Substudy of WHI *
Event | Relative Risk CE vs . Placebo (95% nCI†) | CE n = 5,310 | Placebo n = 5,429
 |  | Absolute Risk per 10,000 Women-Years
CHD events ‡ Non-fatal MI ‡ CHD death ‡ | 0.95 (0.78-1.16) 0.91 (0.73-1.14) 1.01 (0.71-1.43) | 54 40 16 | 57 43 16
All strokes ‡ Ischemic stroke ‡ | 1.33 (1.05-1.68) 1.55 (1.19-2.01) | 45 38 | 33 25
Deep vein thrombosis ‡§ | 1.47 (1.06-2.06) | 23 | 15
Pulmonary embolism ‡ | 1.37 (0.90-2.07) | 14 | 10
Invasive breast cancer ‡ | 0.80 (0.62-1.04) | 28 | 34
Colorectal cancer ‡ | 1.08 (0.75-1.55) | 17 | 16
Hip fracture ‡ | 0.65 (0.45-0.94) | 12 | 19
Vertebral fractures ‡§ | 0.64 (0.44-0.93) | 11 | 18
Lower arm/wrist fracture ‡§ | 0.58 (0.47-0.72) | 35 | 59
Total fractures ‡§ | 0.71 (0.64-0.80) | 144 | 197
Death due to other causes ¶# | 1.08 (0.88-1.32) | 53 | 50
Overall mortality ‡§ | 1.04 (0.88-1.22) | 79 | 75
Global index Ꝥ | 1.02 (0.92-1.13) | 206 | 201
*Adapted from numerous WHI publications. WHI publications can be viewed at
www.nhlbi.nih.gov/whi.
† Nominal confidence intervals unadjusted for multiple looks and multiple comparisons.
‡ Results are based on centrally adjudicated data for an average follow-up of 7.1 years.
§ Not included in “global index”.
¶Results are based on an average follow-up of 6.8 years.
# All deaths, except from breast or colorectal cancer, definite or probable CHD, PE or
cerebrovascular disease.
Ꝥ A subset of the events was combined in a "global index," defined as the earliest occurrence of
CHD events, invasive breast cancer, stroke, pulmonary embolism, endometrial cancer,
colorectal cancer, hip fracture, or death due to other causes.

For those outcomes included in the WHI “global index” that reached statistical significance, the absolute excess risk per 10,000 women-years in the group treated with CE-alone was 12 more strokes, while the absolute risk reduction per 10,000 women-years was 7 fewer hip fractures.^9 The absolute excess risk of events included in the "global index" was a non-significant 5 events per 10,000 women-years. There was no difference between the groups in terms of all-cause mortality.

No overall difference for primary CHD events (nonfatal MI, silent MI, and CHD death) and invasive breast cancer in women receiving CE-alone compared with placebo was reported in final centrally adjudicated results from the estrogen-alone substudy, after an average follow-up of 7.1 years. See Table 3.

Centrally adjudicated results for stroke events from the estrogen-alone substudy, after an average follow-up of 7.1 years, reported no significant difference in the distribution of stroke subtype or severity, including fatal strokes, in women receiving CE-alone compared to placebo. Estrogen-alone therapy increased the risk of ischemic stroke, and this excess risk was present in all subgroups of women examined.^10

Timing of initiation of estrogen-alone therapy relative to the start of menopause may affect the overall risk benefit profile. The WHI estrogen-alone substudy stratified by age showed in women 50 to 59 years of age a non-significant trend toward reduced risk for CHD [hazard ratio (HR) 0.63 (95 percent CI, 0.36-1.09)] and overall mortality [HR 0.71 (95 percent CI, 0.46-1.11)].

WHI Estrogen Plus Progestin Substudy

The WHI estrogen plus progestin substudy was stopped early. According to the predefined stopping rule, after an average follow-up of 5.6 years of treatment, the increased risk of invasive breast cancer and cardiovascular events exceeded the specified benefits included in the “global index.” The absolute excess risk of events included in the “global index” was 19 per 10,000 women-years.

For those outcomes included in the WHI “global index” that reached statistical significance after 5.6 years of follow-up, the absolute excess risks per 10,000 women-years in the group treated with CE plus MPA were 7 more CHD events, 8 more strokes, 10 more PEs, and 8 more invasive breast cancers, while the absolute risk reduction per 10,000 women-years were 6 fewer colorectal cancers and 5 fewer hip fractures.

Results of the CE plus MPA substudy, which included 16,608 women (average 63 years of age, range 50-79; 83.9 percent White, 6.8 percent Black, 5.4 percent Hispanic, 3.9 percent Other), are presented in Table 4. These results reflect centrally adjudicated data after an average follow-up of 5.6 years.

Table 4: Relative and Absolute Risk Seen in the Estrogen Plus Progestin Substudy of WHI at an Average of 5.6 Years *†
Event | Relative Risk CE/MPA vs . Placebo (95% nCI‡) | CE/MPA n = 8,506 | Placebo n = 8,102
 | Relative Risk CE/MPA vs . Placebo (95% nCI‡) | Absolute Risk per 10,000 Women-Years
CHD events Non-fatal MI CHD death | 1.23 (0.99-1.53) 1.28 (1.00-1.63) 1.10 (0.70-1.75) | 41 31 8 | 34 25 8
All strokes Ischemic stroke | 1.31 (1.03-1.68) 1.44 (1.09-1.90) | 33 26 | 25 18
Deep vein thrombosis § | 1.95 (1.43-2.67) | 26 | 13
Pulmonary embolism | 2.13 (1.45-3.11) | 18 | 8
Invasive breast cancer ¶ | 1.24 (1.01-1.54) | 41 | 33
Colorectal cancer | 0.61 (0.42-0.87) | 10 | 16
Endometrial cancer § | 0.81 (0.48-1.36) | 6 | 7
Cervical cancer § | 1.44 (0.47-4.42) | 2 | 1
Hip fracture | 0.67 (0.47-0.96) | 11 | 16
Vertebral fractures § | 0.65 (0.46-0.92) | 11 | 17
Lower arm/wrist fractures § | 0.71 (0.59-0.85) | 44 | 62
Total fractures | 0.76 (0.69-0.83) | 152 | 199
Overall mortality # | 1.00 (0.83-1.19) | 52 | 52
Global Index Ꝥ | 1.13 (1.02-1.25) | 184 | 165
* Adapted from numerous WHI publications. WHI publications can be viewed at
www.nhlbi.nih.gov/whi.
† Results are based on centrally adjudicated data.
‡ Nominal confidence intervals unadjusted for multiple looks and multiple comparisons.
§ Not included in “global index”.
¶ Includes metastatic and non-metastatic breast cancer, with the exception of in-situ breast
cancer.
# All deaths, except from breast or colorectal cancer, definite or probable CHD, PE or
cerebrovascular disease.
Ꝥ A subset of the events was combined in a "global index," defined as the earliest occurrence of
CHD events, invasive breast cancer, stroke, pulmonary embolism, endometrial cancer,
colorectal cancer, hip fracture, or death due to other causes.

Timing of initiation of estrogen plus progestin therapy relative to the start of menopause may affect the overall risk benefit profile. The WHI estrogen plus progestin substudy stratified by age showed in women 50 to 59 years of age a non-significant trend toward reduced risk for overall mortality [HR 0.69 (95 percent CI, 0.44-1.07)].

14.4 Women's Health Initiative Memory Study

The WHIMS estrogen-alone ancillary study of WHI enrolled 2,947 predominantly healthy hysterectomized postmenopausal women 65 years of age and older (45 percent were 65 to 69 years of age, 36 percent were 70 to 74 years of age, and 19 percent were 75 years of age and older) to evaluate the effects of daily CE (0.625 mg)-alone on the incidence of probable dementia (primary outcome) compared to placebo.

After an average follow-up of 5.2 years, the relative risk of probable dementia for CE-alone versus placebo was 1.49 (95 percent CI, 0.83-2.66). The absolute risk of probable dementia for CE-alone versus placebo was 37 versus 25 cases per 10,000 women-years. Probable dementia as defined in the study included Alzheimer’s disease (AD), vascular dementia (VaD) and mixed type (having features of both AD and VaD). The most common classification of probable dementia in the treatment group and the placebo group was AD. Since the ancillary study was conducted in women 65 to 79 years of age, it is unknown whether these findings apply to younger postmenopausal women [see Warnings and Precautions (5.3), and Use in Specific Populations (8.5)].

The WHIMS estrogen plus progestin ancillary study enrolled 4,532 predominantly healthy postmenopausal women 65 years of age and older (47 percent were 65 to 69 years of age, 35 percent were 70 to 74 years of age, and 18 percent were 75 years of age and older) to evaluate the effects of daily CE (0.625 mg) plus MPA (2.5 mg) on the incidence of probable dementia (primary outcome) compared to placebo.

After an average follow-up of 4 years, the relative risk of probable dementia for CE plus MPA versus placebo was 2.05 (95 percent CI, 1.21-3.48). The absolute risk of probable dementia for CE plus MPA versus placebo was 45 versus 22 cases per 10,000 women-years. Probable dementia as defined in the study included AD, VaD and mixed type (having features of both AD and VaD). The most common classification of probable dementia in the treatment group and the placebo group was AD. Since the ancillary study was conducted in women 65 to 79 years of age, it is unknown whether these findings apply to younger postmenopausal women [see Warnings and Precautions (5.3), and Use in Specific Populations (8.5)].

When data from the two populations were pooled as planned in the WHIMS protocol, the reported overall relative risk for probable dementia was 1.76 (95 percent CI, 1.19-2.60). Differences between groups became apparent in the first year of treatment. It is unknown whether these findings apply to younger postmenopausal women [see Warnings and Precautions (5.3), and Use in Specific Populations (8.5)].

15 REFERENCES

1. Rossouw JE, et al. Postmenopausal Hormone Therapy and Risk of Cardiovascular Disease by Age and Years Since Menopause. JAMA. 2007;297:1465-1477.
2. Hsia J, et al. Conjugated Equine Estrogens and Coronary Heart Disease. Arch Int Med. 2006;166:357-365.
3. Curb JD, et al. Venous Thrombosis and Conjugated Equine Estrogen in Women Without a Uterus. Arch Int Med. 2006;166:772-780.
4. Cushman M, et al. Estrogen Plus Progestin and Risk of Venous Thrombosis. JAMA. 2004;292:1573-1580.
5. Stefanick ML, et al. Effects of Conjugated Equine Estrogens on Breast Cancer and Mammography Screening in Postmenopausal Women With Hysterectomy. JAMA. 2006;295:1647-1657.
6. Chlebowski RT, et al. Influence of Estrogen Plus Progestin on Breast Cancer and Mammography in Healthy Postmenopausal Women. JAMA. 2003;289:3234-3253.
7. Anderson GL, et al. Effects of Estrogen Plus Progestin on Gynecologic Cancers and Associated Diagnostic Procedures. JAMA. 2003;290:1739-1748.
8. Shumaker SA, et al. Conjugated Equine Estrogens and Incidence of Probable Dementia and Mild Cognitive Impairment in Postmenopausal Women. JAMA. 2004;291:2947-2958.
9. Jackson RD, et al. Effects of Conjugated Equine Estrogen on Risk of Fractures and BMD in Postmenopausal Women With Hysterectomy: Results From the Women's Health Initiative Randomized Trial. J Bone Miner Res. 2006;21:817-828.
10. Hendrix SL, et al. Effects of Conjugated Equine Estrogen on Stroke in the Women's Health Initiative. Circulation. 2006;113:2425-2434.

16 HOW SUPPLIED/STORAGE AND HANDLING

16.1 How Supplied

Estradiol gel is a clear, colorless, hydroalcoholic 0.06 percent estradiol gel supplied in a non-aerosol, metered-dose pump. The pump consists of an LDPE inner liner encased in rigid plastic with a resealable polypropylene cap. Estradiol gel, 0.06% is available in a 50-gram (1.75 oz) size. Each individually packaged 50-gram pump contains 50 grams of gel and can deliver 30 metered 1.25-g doses.

NDC: 73473-308-50............................. (50-gram pump)

16.2 Storage and Handling

Keep out of reach of children.

Store at 20° to 25°C (68° to 77°F); excursions permitted to 15° to 30°C (59° to 86°F) [See USP Controlled Room Temperature].

17 PATIENT COUNSELING INFORMATION

Advise women to read the FDA-approved patient labeling (Patient Information and Instructions for Use)

Vaginal Bleeding

Inform postmenopausal women to report any vaginal bleeding to their healthcare provider as soon as possible [see Warnings and Precautions (5.2)].

Possible Serious Adverse Reactions with Estrogen-Alone Therapy

Inform postmenopausal women of the possible serious adverse reactions of estrogen-alone therapy including Cardiovascular Disorders, Malignant Neoplasms, and Probable Dementia [see Warnings and Precautions (5.1, 5.2, 5.3)].

Possible Common Adverse Reactions with Estrogen-Alone Therapy

Inform postmenopausal women of possible less serious but common adverse reactions of estrogen-alone therapy such as headache, breast pain and tenderness, nausea, and vomiting.

Manufactured for:
Solaris Pharma Corporation
Bridgewater, NJ 08807

Patient Information

Estradiol Gel, 0.06% (ES-tra-DYE-ol jĕl)

Read this Patient Information before you start using estradiol gel, and each time you get a refill. There may be new information. This information does not take the place of talking to your healthcare provider about your menopausal symptoms or your treatment.

What is the most important information I should know about estradiol gel (an estrogen hormone)?

- Using estrogen-alone may increase your chance of getting cancer of the uterus (womb). Report any unusual vaginal bleeding right away while you are using estradiol gel. Vaginal bleeding after menopause may be a warning sign of cancer of the uterus (womb). Your healthcare provider should check any unusual vaginal bleeding to find out the cause.
- Do not use estrogen-alone to prevent heart disease, heart attacks, strokes or dementia (decline in brain function).
- Using estrogen-alone may increase your chances of getting strokes and blood clots.
- Using estrogen-alone may increase your chance of getting dementia, based on a study of women 65 years of age and older.
- Do not use estrogens with progestogens to prevent heart disease, heart attack, strokes or dementia.
- Using estrogens with progestogens may increase your chances of getting heart attacks, strokes, breast cancer, or blood clots.
- Using estrogens with progestogens may increase your chance of getting dementia, based on a study of women 65 years of age and older.
- Only one estrogen-alone product and dose have been shown to increase your chances of getting strokes, blood clots, and dementia. Only one estrogen with progestogen product and dose have been shown to increase your chances of getting heart attacks, strokes, breast cancer, blood clots, and dementia. Because other products and doses have not been studied in the same way, it is not known how the use of estradiol gel will affect your chances of these conditions. You and your healthcare provider should talk regularly about whether you still need treatment with estradiol gel.

What is estradiol gel?

Estradiol gel is a prescription medicine gel that contains estradiol (an estrogen hormone).

What is estradiol gel used for?

Estradiol gel is used after menopause to:

- Reduce moderate to severe hot flashes

Estrogens are hormones made by a woman’s ovaries. The ovaries normally stop making estrogens when a woman is between 45 and 55 years old. This drop in body estrogen levels causes the “change of life” or menopause (the end of monthly menstrual periods). Sometimes, both ovaries are removed during an operation before natural menopause takes place. The sudden drop in estrogen levels causes “surgical menopause."

When the estrogen levels begin dropping, some women develop very uncomfortable symptoms, such as feelings of warmth in the face, neck, and chest, or sudden intense feelings of heat and sweating (“hot flashes” or “hot flushes”). In some women, the symptoms are mild, and they will not need to use estrogens. In other women, symptoms can be more severe.

- Treat moderate to severe menopausal changes in and around the vagina

You and your healthcare provider should talk regularly about whether you need treatment with estradiol gel to control these problems. If you use estradiol gel only to treat your menopausal changes in and around your vagina, talk with your healthcare provider about whether a topical vaginal product would be better for you.

Who should not use estradiol gel?

Do not start using estradiol gel if you:

- have unusual vaginal bleeding

Vaginal bleeding after menopause may be a warning sign of cancer of the uterus (womb). Your healthcare provider should check any unusual vaginal bleeding to find out the cause.

- have been diagnosed with a bleeding disorder
- currently have or have had certain cancers

Estrogens may increase the chance of getting certain types of cancer, including cancer of the breast or uterus. If you have or have had cancer, talk with your healthcare provider about whether you should use estradiol gel.

- had a stroke or heart attack
- currently have or have had blood clots
- currently have or have had liver problems
- are allergic to estradiol gel or any of its ingredients

See the list of ingredients in estradiol gel at the end of this leaflet.

Before you use estradiol gel, tell your healthcare provider about all of your medical conditions, including if you:

- have any unusual vaginal bleeding

Vaginal bleeding after menopause may be a warning sign of cancer of the uterus (womb). Your healthcare provider should check any unusual vaginal bleeding to find out the cause.

- have any other medical conditions that may become worse while you are using estradiol gel

Your healthcare provider may need to check you more carefully if you have certain conditions, such as asthma (wheezing), epilepsy (seizures), diabetes, migraine, endometriosis, lupus, angioedema (swelling of face and tongue), problems with your heart, liver, thyroid, kidneys, or high calcium levels in your blood.

- are going to have surgery or will be on bed rest

Your healthcare provider will let you know if you need to stop using estradiol gel.

- are pregnant or think you may be pregnant

Estradiol gel is not for pregnant women.

- are breastfeeding

The hormone in estradiol gel can pass into your breast milk.

Tell your healthcare provider about all the medicines you take, including prescription and over-the-counter medicines, vitamins, and herbal supplements. Some medicines may affect how estradiol gel works. Estradiol gel may also affect how your other medicines work. Keep a list of your medicines and show it to your healthcare provider and pharmacist when you get a new medicine.

How should I use estradiol gel?

For detailed instructions, see the step-by-step instructions for using estradiol gel at the end of this Patient Information.

- Use estradiol gel exactly as your healthcare provider tells you to use it.
- Estradiol gel is for skin use only.
- Estradiol gel contains alcohol, which is flammable. Avoid fire, flame or smoking until estradiol gel has dried.
- You and your healthcare provider should talk regularly (for example, every 3 to 6 months) about the dose you are using and whether you still need treatment with estradiol gel.

What are the possible side effects of estradiol gel?

Side effects are grouped by how serious they are and how often they happen when you are treated.

Serious, but less common side effects include:

- heart attack
- stroke
- blood clots
- breast cancer
- cancer of the lining of the uterus (womb)
- cancer of the ovary
- dementia
- high or low blood calcium
- gallbladder disease
- visual abnormalities
- high blood pressure
- high levels of fat (triglycerides) in your blood
- liver problems
- changes in your thyroid hormone levels
- fluid retention
- cancer changes of endometriosis
- enlargement of benign tumors of the uterus (“fibroids”)
- worsening of swelling of face and tongue (angioedema) in women with a history of angioedema
- changes in laboratory test results such as bleeding time and high blood sugar

Call your healthcare provider right away if you get any of the following warning signs or any other unusual symptoms that concern you:

- new breast lumps
- unusual vaginal bleeding
- changes in vision or speech
- sudden new severe headaches
- severe pains in your chest or legs with or without shortness of breath, weakness and fatigue
- swelling of face, lips, and tongue with or without red, itchy bumps

Common side effects of estradiol gel include:

- headache
- breast tenderness or pain
- stomach or abdominal cramps, bloating
- nausea and vomiting
- hair loss
- fluid retention
- vaginal yeast infection

These are not all of the possible side effects of estradiol gel. For more information, ask your healthcare provider or pharmacist. Tell your healthcare provider if you have any side effects that bother you or do not go away. You may report side effects to Solaris Pharma Corporation at 1-833-919-0527 or to FDA at 1-800-FDA-1088.

What can I do to lower my chances of a serious side effect with estradiol gel?

- Talk with your healthcare provider regularly about whether you should continue using estradiol gel.
- If you have a uterus, talk with your healthcare provider about whether the addition of a progestogen is right for you.
- In general, the addition of a progestogen is recommended for women with a uterus to reduce the chance of getting cancer of the uterus (womb).
- See your healthcare provider right away if you get vaginal bleeding while using estradiol gel.
- Have a pelvic exam, breast exam and mammogram (breast x-ray) every year unless your healthcare provider tells you something else.
- If members of your family have had breast cancer or if you have ever had breast lumps or an abnormal mammogram (breast x-ray), you may need to have breast exams more often.
- If you have high blood pressure, high cholesterol (fat in the blood), diabetes, are overweight, or if you use tobacco, you may have higher chances of getting heart disease.

Ask your healthcare provider for ways to lower your chances of getting heart disease.

How should I store estradiol gel?

- Store estradiol gel at room temperature between 68°F to 77°F (20°C to 25°C).

Keep estradiol gel and all medicines out of the reach of children.

General information about the safe and effective use of estradiol gel

Medicines are sometimes prescribed for conditions that are not mentioned in Patient Information leaflets. Do not use estradiol gel for conditions for which it was not prescribed. Do not give estradiol gel to other people, even if they have the same symptoms you have. It may harm them.

You can ask your healthcare provider or pharmacist for information about estradiol gel that is written for health professionals.

For more information, go to www.solaris-pharma.com, or call Solaris Pharma Corporation at 1-833-919-0527.

What are the ingredients in estradiol gel?

Active ingredient: estradiol

Inactive ingredients: purified water, alcohol (44.89% v/v), triethanolamine, and carbomer 974P.

Instructions for Use

Estradiol Gel, 0.06% (ES-tra-DYE-ol jĕl)

Read this Instructions for Use before you start using estradiol gel and each time you get a refill. There may be new information. This information does not take the place of talking to your healthcare provider about your menopausal symptoms or your treatment.

You will need the following supplies to use estradiol gel: See Figure A.

Figure A

Estradiol gel is supplied in a metered-dose pump that delivers a measured amount of estradiol to your skin each time you press the pump.

Estradiol gel is available in a 50-gram canister.

Step 1. Priming the estradiol gel pump

- Before using the estradiol gel pump for the first time, the pump must be primed. The estradiol gel canister contains enough medicine to allow you to prime the pump before you use it for the first time.
- Remove the large cap from the canister. See Figure B.

Figure B

- Slowly push the pump all the way down 5 times. Do not use any estradiol gel that came out while priming. Wash it down the sink to avoid accidental exposure to others.
- After priming, the estradiol gel pump is ready to use. One complete press of the pump will give the same amount of estradiol gel each time.

Step 2. Applying estradiol gel to your skin

- Do not allow other people to apply estradiol gel to your skin for you.
- Apply estradiol gel to clean, dry, unbroken skin.
- Apply estradiol gel after your bath or shower. If you go swimming, try to leave as much time as possible between using your estradiol gel and going swimming.
- Remove the small cover on the tip of the pump if you have not done so already. See Figure C.

Figure C

- To use estradiol gel, press the estradiol gel pump firmly and fully 1 time into the palm of your hand. See Figure D.

Figure D

- Using your hand, apply estradiol gel to the skin of your other arm. See Figure E.
  Spread the gel as thinly as possible over the entire area on the inside and outside of your arm from your wrist to your shoulder. See Figure F.

Figure E

Figure F

- Do not apply estradiol gel directly to your breasts or in and around your vagina.
- Do not massage or rub in estradiol gel. Allow the gel to dry for 5 minutes before you get dressed.

Step 3. After you use estradiol gel

- Place the small cap back on the tip of the pump. Place the large cap over the top of the canister.
- Wash your hands right away with soap and water after applying estradiol gel. This will lower the chance that the medicine will spread from your hands to other people.
- Do not allow others to make contact with the area of skin where you applied the gel for at least 1 hour after application.
- Estradiol gel is flammable until dry. Let estradiol gel dry before smoking or going near an open flame.

Step 4. Throwing away used estradiol gel canisters

- The estradiol gel 50-gram canister contains enough medicine to allow for priming your canister with up to 5 full pump depressions and delivery of 30 daily doses. After you have first primed your canister and used 30 doses, you will need to throw away the canister. Do not use the canister for more than 30 doses even though the canister may not be completely empty. You may not get the correct dose.

This Patient Information and Instructions for Use has been approved by the U.S. Food and Drug Administration.

Manufactured for:
Solaris Pharma Corporation
Bridgewater, NJ 08807

Revised: 04/2024

17.2 FDA-approved patient labeling

.

SPL PATIENT PACKAGE INSERT SECTION

.

PACKAGE LABEL.PRINCIPAL DISPLAY PANEL

50 grams Carton Label

NDC 73473-308-50
Estradiol Gel, 0.06%
For topical use only

A multiple-dose pump containing 50 grams (1.75 oz)

Rx only
50 grams